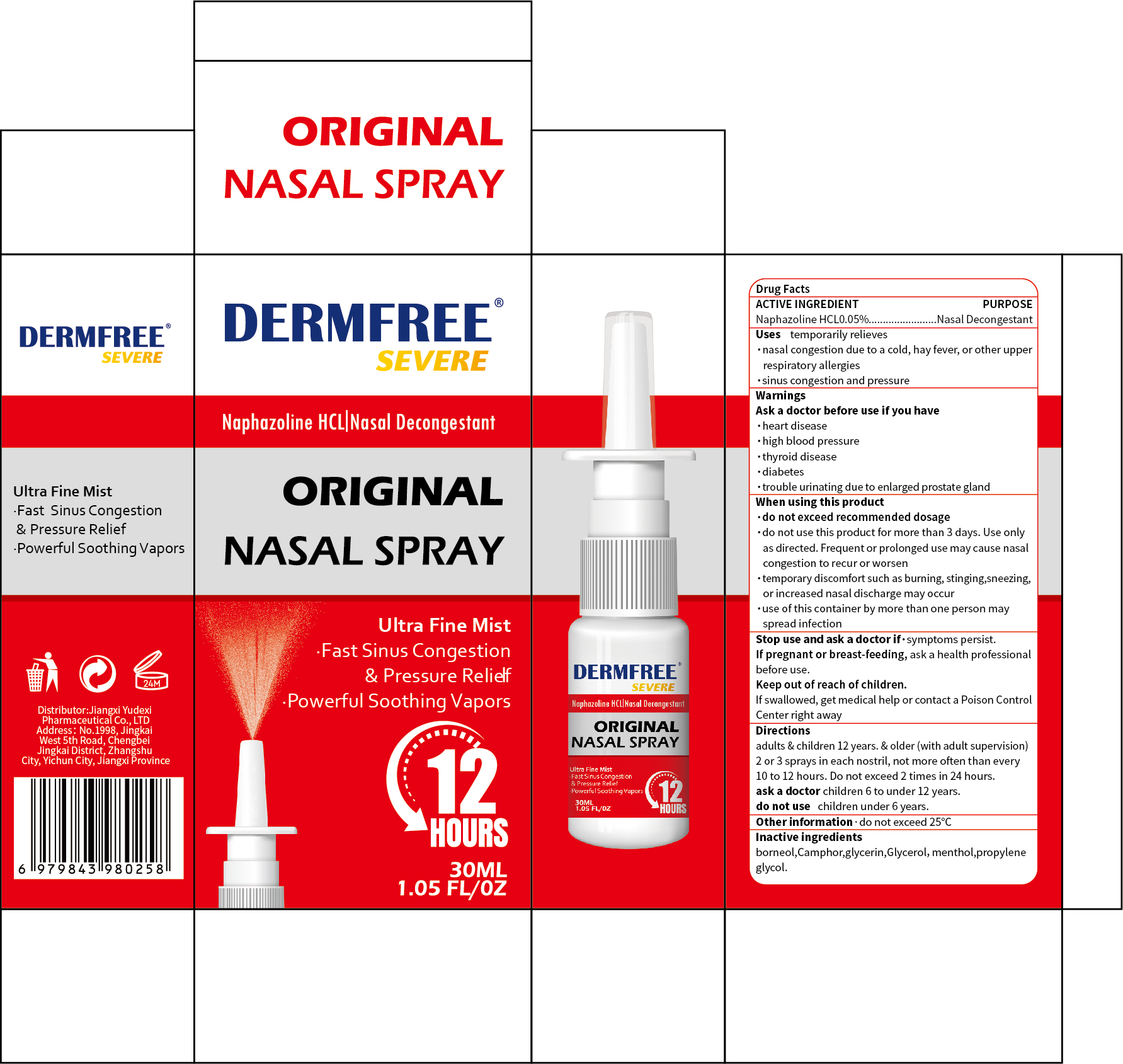 DRUG LABEL: DERMFREE ORIGINAL NASAL
NDC: 85248-111 | Form: SPRAY
Manufacturer: Jiangxi Yudexi Pharmaceutical Co., LTD
Category: otc | Type: HUMAN OTC DRUG LABEL
Date: 20260208

ACTIVE INGREDIENTS: NAPHAZOLINE HCL 0.05 g/100 mL
INACTIVE INGREDIENTS: CAMPHOR (SYNTHETIC); MENTHOL; BORNEOL; GLYCERIN; PROPYLENE GLYCOL

85248-111

Active Ingredient

Naphazoline HCL 0.05%.

Purpose

Nasal Decongestant

Use

temporarily relieves .nasal congestion due to a cold, hay fever, or other upper respiratory allergies .sinus congestion and pressure

Warnings

Ask a doctor before use if you have
·heart disease·high blood pressure·thyroid disease·diabetes·trouble urinating due to enlarged prostate gland

.Do not use this product for more than 3 days.Use only as directed. Frequent or prolonged use may cause nasal congestion to recur or worsen. .Temporary discomfort such as burning,stinging,sneezing,or increased nasal discharge may occur.
·Use of this container by more than one person may spread infection. children under 6 years.

When Using

When using this product
.Do not exceed recommended dosage
.Do not use this product for more than 3 days.Use only as directed. Frequent or prolonged use may cause nasal congestion to recur or worsen. .Temporary discomfort such as burning,stinging,sneezing,or increased nasal discharge may occur.
·Use of this container by more than one person may spread infection.

Stop Use

Stop use and ask a doctor if .symptoms persist
.If pregnant or breast-feeding, ask a health professionalbefore use.

Ask Doctor

. children 6 to under 12 years.
.if symptoms persist
.If pregnant or breast-feeding, ask a health professionalbefore use.

Keep Oot Of Reach Of Children

if swallowed, get medical help or contact a Poison Control Center right away.

Directions

Adults&children 12 years & older(with adult supervision): 2 or 3 sprays in each nostril,not more often than every 10 to 12 hours. Do not exceed 2 times in 24 hours.
Ask a doctor: children 6 to under 12 years,Do not use children under 6 years.

Other information

do not exceed 25°C

Inactive ingredients

borneol,Camphor,glycerin,Glycerol,menthol,propylene glycol